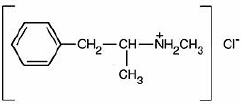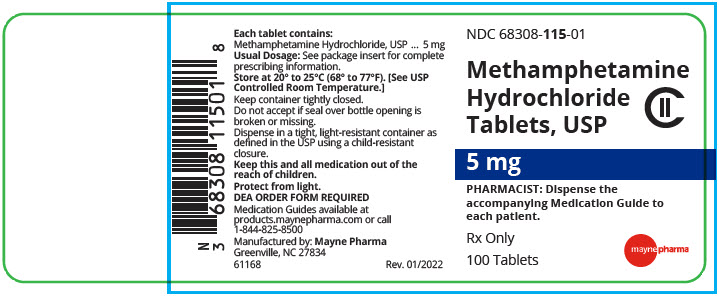 DRUG LABEL: Methamphetamine Hydrochloride
NDC: 68308-115 | Form: TABLET
Manufacturer: Mayne Pharma Commercial LLC
Category: prescription | Type: HUMAN PRESCRIPTION DRUG LABEL
Date: 20230705
DEA Schedule: CII

ACTIVE INGREDIENTS: METHAMPHETAMINE HYDROCHLORIDE 5 mg/1 1
INACTIVE INGREDIENTS: STARCH, CORN; LACTOSE MONOHYDRATE; STEARIC ACID; TALC

Methamphetamine Hydrochloride Tablets, USP

5 mg
CII

Rxonly

BOXED WARNING

METHAMPHETAMINE HAS A HIGH POTENTIAL FOR ABUSE. PARTICULAR ATTENTION SHOULD BE PAID TO THE POSSIBILITY OF SUBJECTS OBTAINING METHAMPHETAMINE FOR NON-THERAPEUTIC USE OR DISTRIBUTION TO OTHERS, AND THE DRUG SHOULD BE PRESCRIBED OR DISPENSED SPARINGLY. MISUSE OF METHAMPHETAMINE MAY CAUSE SUDDEN DEATH AND SERIOUS CARDIOVASCULAR ADVERSE EVENTS.

DESCRIPTION

Methamphetamine hydrochloride tablets, USP chemically known as (S)-N, α -dimethylbenzeneethanamine hydrochloride, is a member of the amphetamine group of sympathomimetic amines. It has the following structural formula:

Methamphetamine hydrochloride tablets contain 5 mg of methamphetamine hydrochloride, USP for oral administration.

Inactive Ingredients

Corn starch, lactose monohydrate, stearic acid and talc.

CLINICAL PHARMACOLOGY

Methamphetamine is a sympathomimetic amine with CNS stimulant activity. Peripheral actions include elevation of systolic and diastolic blood pressures and weak bronchodilator and respiratory stimulant action. Other central nervous system actions, or metabolic effects, may be involved, for example.

The mechanism of action involved in producing the beneficial behavioral changes seen in hyperkinetic children receiving methamphetamine is unknown.

In humans, methamphetamine is rapidly absorbed from the gastrointestinal tract. The primary site of metabolism is in the liver by aromatic hydroxylation, N-dealkylation and deamination. At least seven metabolites have been identified in the urine. The biological half-life has been reported in the range of 4 to 5 hours. Excretion occurs primarily in the urine and is dependent on urine pH. Alkaline urine will significantly increase the drug half-life. Approximately 62% of an oral dose is eliminated in the urine within the first 24 hours with about one-third as intact drug and the remainder as metabolites.

INDICATIONS AND USAGE

Attention Deficit Disorder with Hyperactivity

Methamphetamine hydrochloride tablets are indicated as an integral part of a total treatment program which typically includes other remedial measures (psychological, educational, social) for a stabilizing effect in children over 6 years of age with a behavioral syndrome characterized by the following group of developmentally inappropriate symptoms: moderate to severe distractibility, short attention span, hyperactivity, emotional lability, and impulsivity. The diagnosis of this syndrome should not be made with finality when these symptoms are only of comparatively recent origin. Nonlocalizing (soft) neurological signs, learning disability, and abnormal EEG may or may not be present, and a diagnosis of central nervous system dysfunction may or may not be warranted.

CONTRAINDICATIONS

In patients known to be hypersensitive to amphetamine, or other components of methamphetamine hydrochloride tablets. Hypersensitivity reactions such as angioedema and anaphylactic reactions have been reported in patients treated with other amphetamine products (see ADVERSE REACTIONS).

Patients taking monoamine oxidase inhibitors (MAOIs), or within 14 days of stopping MAOIs (including MAOIs such as linezolid or intravenous methylene blue), because of an increased risk of hypertensive crisis (see WARNINGSand DRUG INTERACTIONS). It is also contraindicated in patients with glaucoma, advanced arteriosclerosis, symptomatic cardiovascular disease, moderate to severe hypertension, hyperthyroidism or known hypersensitivity or idiosyncrasy to sympathomimetic amines. Methamphetamine should not be given to patients who are in an agitated state or who have a history of drug abuse.

WARNINGS

Serious Cardiovascular Events

Sudden Death and Pre-existing Structural Cardiac Abnormalities or Other Serious Heart Problems

- Children and Adolescents: Sudden death has been reported in association with CNS stimulant treatment at usual doses in children and adolescents with structural cardiac abnormalities or other serious heart problems. Although some serious heart problems alone carry an increased risk of sudden death, stimulant products generally should not be used in children or adolescents with known serious structural cardiac abnormalities, cardiomyopathy, serious heart rhythm abnormalities, or other serious cardiac problems that may place them at increased vulnerability to the sympathomimetic effects of a stimulant drug.
- Adults: Sudden deaths, stroke, and myocardial infarction have been reported in adults taking stimulant drugs at usual doses for ADHD. Although the role of stimulants in these adult cases is also unknown, adults have a greater likelihood than children of having serious structural cardiac abnormalities, cardiomyopathy, serious heart rhythm abnormalities, coronary artery disease, or other serious cardiac problems. Adults with such abnormalities should also generally not be treated with stimulant drugs.

Hypertension and other Cardiovascular Conditions

Stimulant medications cause a modest increase in average blood pressure (about 2-4 mmHg) and average heart rate (about 3-6 bpm), and individuals may have larger increases. While the mean changes alone would not be expected to have short-term consequences, all patients should be monitored for larger changes in heart rate and blood pressure. Caution is indicated in treating patients whose underlying medical conditions might be compromised by increases in blood pressure or heart rate, e.g., those with pre-existing hypertension, heart failure, recent myocardial infarction, or ventricular arrhythmia.

Assessing Cardiovascular Status in Patients being Treated with Stimulant Medications

Children, adolescents, or adults who are being considered for treatment with stimulant medications should have a careful history (including assessment for a family history of sudden death or ventricular arrhythmia) and physical exam to assess for the presence of cardiac disease, and should receive further cardiac evaluation if findings suggest such disease (e.g., electrocardiogram and echocardiogram). Patients who develop symptoms such as exertional chest pain, unexplained syncope, or other symptoms suggestive of cardiac disease during stimulant treatment should undergo a prompt cardiac evaluation.

Psychiatric Adverse Events

Pre-existing Psychosis

Administration of stimulants may exacerbate symptoms of behavior disturbance and thought disorder in patients with a pre-existing psychotic disorder.

Bipolar Illness

Particular care should be taken in using stimulants to treat ADHD in patients with comorbid bipolar disorder because of concern for possible induction of a mixed/manic episode in such patients. Prior to initiating treatment with a stimulant, patients with comorbid depressive symptoms should be adequately screened to determine if they are at risk for bipolar disorder; such screening should include a detailed psychiatric history, including a family history of suicide, bipolar disorder, and depression.

Emergence of New Psychotic or Manic Symptoms

Treatment emergent psychotic or manic symptoms, e.g., hallucinations, delusional thinking, or mania in children and adolescents without a prior history of psychotic illness or mania can be caused by stimulants at usual doses. If such symptoms occur, consideration should be given to a possible causal role of the stimulant, and discontinuation of treatment may be appropriate. In a pooled analysis of multiple short-term, placebo-controlled studies, such symptoms occurred in about 0.1% (4 patients with events out of 3,482 exposed to methylphenidate or amphetamine for several weeks at usual doses) of stimulant-treated patients compared to 0 in placebo-treated patients.

Aggression

Aggressive behavior or hostility is often observed in children and adolescents with ADHD, and has been reported in clinical trials and the postmarketing experience of some medications indicated for the treatment of ADHD. Although there is no systematic evidence that stimulants cause aggressive behavior or hostility, patients beginning treatment for ADHD should be monitored for the appearance of or worsening of aggressive behavior or hostility.

Long-Term Suppression of Growth

Careful follow-up of weight and height in children ages 7 to 10 years who were randomized to either methylphenidate or non-medication treatment groups over 14 months, as well as in naturalistic subgroups of newly methylphenidate-treated and non-medication treated children over 36 months (to the ages of 10 to 13 years), suggests that consistently medicated children (i.e., treatment for 7 days per week throughout the year) have a temporary slowing in growth rate (on average, a total of about 2 cm less growth in height and 2.7 kg less growth in weight over 3 years), without evidence of growth rebound during this period of development. Published data are inadequate to determine whether chronic use of amphetamines may cause a similar suppression of growth, however, it is anticipated that they likely have this effect as well. Therefore, growth should be monitored during treatment with stimulants, and patients who are not growing or gaining height or weight as expected may need to have their treatment interrupted.

Seizures

There is some clinical evidence that stimulants may lower the convulsive threshold in patients with prior history of seizures, in patients with prior EEG abnormalities in absence of seizures, and, very rarely, in patients without a history of seizures and no prior EEG evidence of seizures. In the presence of seizures, the drug should be discontinued.

Peripheral Vasculopathy, including Raynaud's phenomenon

Stimulants, including methamphetamine hydrochloride tablets, used to treat ADHD are associated with peripheral vasculopathy, including Raynaud's phenomenon. Signs and symptoms are usually intermittent and mild; however, very rare sequelae include digital ulceration and/or soft tissue breakdown. Effects of peripheral vasculopathy, including Raynaud's phenomenon, were observed in post-marketing reports at different times and at therapeutic doses in all age groups throughout the course of treatment. Signs and symptoms generally improve after reduction in dose or discontinuation of drug. Careful observation for digital changes is necessary during treatment with ADHD stimulants. Further clinical evaluation (e.g., rheumatology referral) may be appropriate for certain patients.

Serotonin Syndrome

Serotonin syndrome, a potentially life-threatening reaction, may occur when amphetamines are used in combination with other drugs that affect the serotonergic neurotransmitter systems such as monoamine oxidase inhibitors (MAOIs), selective serotonin reuptake inhibitors (SSRIs), serotonin norepinephrine reuptake inhibitors (SNRIs), triptans, tricyclic antidepressants, fentanyl, lithium, tramadol, tryptophan, buspirone, and St. John's Wort (see DRUG INTERACTIONS). Amphetamines and amphetamine derivatives are known to be metabolized, to some degree, by cytochrome P450 2D6 (CYP2D6) and display minor inhibition of CYP2D6 metabolism (see CLINICAL PHARMACOLOGY). The potential for a pharmacokinetic interaction exists with the co-administration of CYP2D6 inhibitors which may increase the risk with increased exposure to methamphetamine hydrochloride tablets. In these situations, consider an alternative nonserotonergic drug or an alternative drug that does not inhibit CYP2D6 (see DRUG INTERACTIONS).

Serotonin syndrome symptoms may include mental status changes (e.g., agitation, hallucinations, delirium, and coma), autonomic instability (e.g., tachycardia, labile blood pressure, dizziness, diaphoresis, flushing, hyperthermia), neuromuscular symptoms (e.g., tremor, rigidity, myoclonus, hyperreflexia, incoordination), seizures, and/or gastrointestinal symptoms (e.g., nausea, vomiting, diarrhea).

Concomitant use of methamphetamine hydrochloride tablets with MAOI drugs is contraindicated (see CONTRAINDICATIONS).

Discontinue treatment with methamphetamine hydrochloride tablets and any concomitant serotonergic agents immediately if the above symptoms occur, and initiate supportive symptomatic treatment. If concomitant use of methamphetamine hydrochloride tablets with other serotonergic drugs or CYP2D6 inhibitors is clinically warranted, initiate methamphetamine hydrochloride tablets with lower doses, monitor patients for the emergence of serotonin syndrome during drug initiation or titration, and inform patients of the increased risk for serotonin syndrome.

Visual Disturbance

Difficulties with accommodation and blurring of vision have been reported with stimulant treatment.

PRECAUTIONS

General

Methamphetamine hydrochloride tablets should be used with caution in patients with even mild hypertension.

Methamphetamine should not be used to combat fatigue or to replace rest in normal persons.

Prescribing and dispensing of methamphetamine should be limited to the smallest amount that is feasible at one time in order to minimize the possibility of overdosage.

Information for Patients

The patient should be informed that methamphetamine may impair the ability to engage in potentially hazardous activities, such as, operating machinery or driving a motor vehicle.

Circulation problems in fingers and toes [Peripheral vasculopathy, including Raynaud's phenomenon]

- Instruct patients beginning treatment with methamphetamine hydrochloride tablets about the risk of peripheral vasculopathy, including Raynaud's Phenomenon, and associated signs and symptoms: fingers or toes may feel numb, cool, painful, and/or may change color from pale, to blue, to red.
- Instruct patients to report to their physician any new numbness, pain, skin color change, or sensitivity to temperature in fingers or toes.
- Instruct patients to call their physician immediately with any signs of unexplained wounds appearing on fingers or toes while taking methamphetamine hydrochloride tablets.
- Further clinical evaluation (e.g., rheumatology referral) may be appropriate for certain patients.

The patient should be cautioned not to increase dosage, except on advice of the physician.

Prescribers or other health professionals should inform patients, their families, and their caregivers about the benefits and risks associated with treatment with methamphetamine and should counsel them in its appropriate use. A patient Medication Guide is available for methamphetamine hydrochloride tablets. The prescriber or health professional should instruct patients, their families, and their caregivers to read the Medication Guide and should assist them in understanding its contents. Patients should be given the opportunity to discuss the contents of the Medication Guide and to obtain answers to any questions they may have.

Drug Interactions

Insulin requirements in diabetes mellitus may be altered in association with the use of methamphetamine and the concomitant dietary regimen.

Methamphetamine may decrease the hypotensive effect of guanethidine.

Methamphetamine hydrochloride tablets should not be used concurrently with monoamine oxidase inhibitors(see CONTRAINDICATIONS).

Concurrent administration of tricyclic antidepressantsand indirect-acting sympathomimetic amines such as the amphetamines, should be closely supervised and dosage carefully adjusted.

Phenothiazinesare reported in the literature to antagonize the CNS stimulant action of the amphetamines.

Drug/Laboratory Test Interactions

Literature reports suggest that amphetamines may be associated with significant elevation of plasma corticosteroids. This should be considered if determination of plasma corticosteroid levels is desired in a person receiving amphetamines.

Acidifying Agents

Lower blood levels and efficacy of amphetamines. Increase dose based on clinical response. Examples of acidifying agents include gastrointestinal acidifying agents (e.g., guanethidine, reserpine, glutamic acid HCl, ascorbic acid) and urinary acidifying agents (e.g., ammonium chloride, sodium acid phosphate, methenamine salts).

Alkalinizing Agents

Increase blood levels and potentiate the action of amphetamine. Co-administration of methamphetamine hydrochloride tablets and gastrointestinal alkalinizing agents should be avoided. Examples of alkalinizing agents include gastrointestinal alkalinizing agents (e.g., sodium bicarbonate) and urinary alkalinizing agents (e.g., acetazolamide, some thiazides).

Tricyclic Antidepressants

May enhance the activity of tricyclic or sympathomimetic agents causing striking and sustained increases in the concentration of d-amphetamine in the brain; cardiovascular effects can be potentiated. Monitor frequently and adjust or use alternative therapy based on clinical response. Examples of tricyclic antidepressants include desipramine, Protriptyline.

CYP2D6 Inhibitors

The concomitant use of methamphetamine hydrochloride tablets and CYP2D6 inhibitors may increase the exposure of methamphetamine hydrochloride tablets compared to the use of the drug alone and increase the risk of serotonin syndrome. Initiate with lower doses and monitor patients for signs and symptoms of serotonin syndrome particularly during methamphetamine hydrochloride tablets initiation and after a dosage increase. If serotonin syndrome occurs, discontinue methamphetamine hydrochloride tablets and the CYP2D6 inhibitor (see WARNINGS, OVERDOSAGE). Examples of CYP2D6 Inhibitors include paroxetine and fluoxetine (also serotonergic drugs), quinidine, ritonavir.

Serotonergic Drugs

The concomitant use of methamphetamine hydrochloride tablets and serotonergic drugs increases the risk of serotonin syndrome. Initiate with lower doses and monitor patients for signs and symptoms of serotonin syndrome, particularly during methamphetamine hydrochloride tablets initiation or dosage increase. If serotonin syndrome occurs, discontinue methamphetamine hydrochloride tablets and the concomitant serotonergic drug(s) (see WARNINGSand PRECAUTIONS). Examples of serotonergic drugs include selective serotonin reuptake inhibitors (SSRI), serotonin norepinephrine reuptake inhibitors (SNRI), triptans, tricyclic antidepressants, fentanyl, lithium, tramadol, tryptophan, buspirone, St. John's Wort.

MAO Inhibitors

Concomitant use of MAOIs and CNS stimulants can cause hypertensive crisis. Potential outcomes include death, stroke, myocardial infarction, aortic dissection, ophthalmological complications, eclampsia, pulmonary edema, and renal failure. Do not administer methamphetamine hydrochloride tablets concomitantly or within 14 days after discontinuing MAOI (see CONTRAINDICATIONSand WARNINGS). Examples of MAOIs include selegiline, tranylcypromine, isocarboxazid, phenelzine, linezolid, methylene blue.

Proton Pump Inhibitors

Time to maximum concentration (Tmax) of amphetamine is decreased compared to when administered alone. Monitor patients for changes in clinical effect and adjust therapy based on clinical response. An example of a proton pump inhibitor is omeprazole.

Carcinogenesis, Mutagenesis, Impairment of Fertility

Data are not available on long-term potential for carcinogenicity, mutagenicity, or impairment of fertility.

Pregnancy

Teratogenic effects

Pregnancy Category C

Methamphetamine has been shown to have teratogenic and embryocidal effects in mammals given high multiples of the human dose. There are no adequate and well-controlled studies in pregnant women. Methamphetamine hydrochloride tablets should not be used during pregnancy unless the potential benefit justifies the potential risk to the fetus.

Nonteratogenic effects

Infants born to mothers dependent on amphetamines have an increased risk of premature delivery and low birth weight. Also, these infants may experience symptoms of withdrawal as demonstrated by dysphoria, including agitation and significant lassitude.

Usage in Nursing Mothers

Amphetamines are excreted in human milk. Mothers taking amphetamines should be advised to refrain from nursing.

Pediatric Use

Long-term effects of methamphetamine in children have not been established (see WARNINGS).

Drug treatment is not indicated in all cases of the behavioral syndrome characterized by moderate to severe distractibility, short attention span, hyperactivity, emotional lability and impulsivity. It should be considered only in light of the complete history and evaluation of the child. The decision to prescribe methamphetamine hydrochloride tablets should depend on the physician's assessment of the chronicity and severity of the child's symptoms and their appropriateness for his/her age. Prescription should not depend solely on the presence of one or more of the behavioral characteristics.

When these symptoms are associated with acute stress reactions, treatment with methamphetamine hydrochloride tablets is usually not indicated.

Clinical experience suggests that in psychotic children, administration of methamphetamine hydrochloride tablets may exacerbate symptoms of behavior disturbance and thought disorder.

Amphetamines have been reported to exacerbate motor and phonic tics and Tourette's syndrome. Therefore, clinical evaluation for tics and Tourette's syndrome in children and their families should precede use of stimulant medications.

Geriatric Use

Clinical Studies of methamphetamine hydrochloride tablets did not include sufficient numbers of subjects age 65 years and over to determine whether elderly subjects respond differently from younger subjects. Other reported clinical experience has not identified differences in responses between the elderly and younger patients. In general, dose selection for an elderly patient should be cautious, usually starting at the low end of the dosing range, reflecting the greater frequency of decreased hepatic, renal or cardiac function, and of concomitant disease or other drug therapy observed in this population.

ADVERSE REACTIONS

The following are adverse reactions in decreasing order of severity within each category that have been reported:

Cardiovascular:Elevation of blood pressure, tachycardia and palpitation. Fatal cardiorespiratory arrest has been reported, mostly in the context of abuse/misuse.

Central Nervous System:Psychotic episodes have been rarely reported at recommended doses. Dizziness, dysphoria, overstimulation, euphoria, insomnia, tremor, restlessness and headache. Exacerbation of motor and phonic tics and Tourette's syndrome.

Gastrointestinal:Diarrhea, constipation, dryness of mouth, unpleasant taste, intestinal ischemia, and other gastrointestinal disturbances.

Hypersensitivity:Urticaria.

Endocrine:Impotence and changes in libido; frequent or prolonged erections.

Musculoskeletal:Rhabdomyolysis.

Miscellaneous:Suppression of growth has been reported with the long-term use of stimulants in children (see WARNINGS).

Skin and Subcutaneous Tissue Disorders:Alopecia.

To report SUSPECTED ADVERSE REACTIONS, contact FDA at 1-800-FDA-1088 or www.fda.gov/medwatchor Mayne Pharma at 1-844-825-8500.

DRUG ABUSE AND DEPENDENCE

Controlled Substance

Methamphetamine hydrochloride tablets are subject to control under DEA schedule II.

Abuse

Methamphetamine has been extensively abused. Tolerance, extreme psychological dependence, and severe social disability have occurred. There are reports of patients who have increased the dosage to many times that recommended. Abrupt cessation following prolonged high dosage administration results in extreme fatigue and mental depression; changes are also noted on the sleep EEG. Manifestations of chronic intoxication with methamphetamine include severe dermatoses, marked insomnia, irritability, hyperactivity, and personality changes. The most severe manifestation of chronic intoxication is psychosis often clinically indistinguishable from schizophrenia. Abuse and/or misuse of methamphetamine have resulted in death. Fatal cardiorespiratory arrest has been reported in the context of abuse and/or misuse of methamphetamine.

OVERDOSAGE

Manifestations of amphetamine overdose include restlessness, tremor, hyperreflexia, rapid respiration, confusion, assaultiveness, hallucinations, panic states, hyperpyrexia, and rhabdomyolysis. Fatigue and depression usually follow the central nervous system stimulation. Serotonin syndrome has also been reported. Cardiovascular effects include arrhythmias, hypertension or hypotension, and circulatory collapse. Gastrointestinal symptoms include nausea, vomiting, diarrhea, and abdominal cramps. Fatal poisoning is usually preceded by convulsions and coma.

Treatment

Consult with a Certified Poison Control Center for up to date guidance and advice.

DOSAGE AND ADMINISTRATION

Methamphetamine hydrochloride tablets are given orally.

Methamphetamine should be administered at the lowest effective dosage, and dosage should be individually adjusted. Late evening medication should be avoided because of the resulting insomnia.

Attention Deficit Disorder with Hyperactivity

For treatment of children 6 years or older with a behavioral syndrome characterized by moderate to severe distractibility, short attention span, hyperactivity, emotional lability and impulsivity:an initial dose of 5 mg methamphetamine hydrochloride tablets once or twice a day is recommended. Daily dosage may be raised in increments of 5 mg at weekly intervals until an optimum clinical response is achieved. The usual effective dose is 20 to 25 mg daily. The total daily dose may be given in two divided doses daily.

Where possible, drug administration should be interrupted occasionally to determine if there is a recurrence of behavioral symptoms sufficient to require continued therapy.

HOW SUPPLIED

Methamphetamine Hydrochloride Tablets, USP are available containing 5 mg of methamphetamine hydrochloride, USP.

The 5 mg tablets are white, round, unscored tablets debossed with 115on one side of the tablet and blank on the other side. They are available as follows:

NDC 68308-115-01
bottles of 100 tablets

STORAGE AND HANDLING

Store at 20° to 25°C (68° to 77°F). [See USP Controlled Room Temperature.]
Protect from light.

Dispense in a tight, light-resistant container as defined in the USP using a child-resistant closure.

Medication Guides available at products.maynepharma.com or call 1-844-825-8500.

Manufactured by:
Mayne Pharma
Greenville, NC 27834

61169
Rev. 03/2022

MEDICATION GUIDE

METHAMPHETAMINE HYDROCHLORIDE TABLETS, USP CII
(metham-fetă-mēn hīdrŏ-klōrīd)

5 mg

Read the Medication Guide that comes with methamphetamine hydrochloride tablets before you or your child starts taking it and each time you get a refill.

There may be new information. This Medication Guide does not take the place of talking to your or your child's doctor about your or your child's treatment with methamphetamine hydrochloride tablets.

What is the most important information I should know about methamphetamine hydrochloride tablets?

The following have been reported with use of methamphetamine hydrochloride and other stimulant medicines.

1. Heart-related problems:

- sudden death in patients who have heart problems or heart defects
- stroke and heart attack in adults
- increased blood pressure and heart rate

Tell your or your child's doctor if you or your child have any heart problems, heart defects, high blood pressure, or a family history of these problems.

Your or your child's doctor should check you or your child carefully for heart problems before starting methamphetamine hydrochloride tablets.

Your or your child's doctor should check you or your child's blood pressure and heart rate regularly during treatment with methamphetamine hydrochloride tablets.

Call your or your child's doctor right away if you or your child has any signs of heart problems such as chest pain, shortness of breath, or fainting while taking methamphetamine hydrochloride tablets.

2. Mental (Psychiatric) problems:

All Patients

- new or worse behavior and thought problems
- new or worse bipolar illness
- new or worse aggressive behavior or hostility

Children and Teenagers

- new psychotic symptoms (such as hearing voices, believing things that are not true, are suspicious) or new manic symptoms

Tell your or your child's doctor about any mental problems you or your child have, or about a family history of suicide, bipolar illness, or depression.

Call your or your child's doctor right away if you or your child have any new or worsening mental symptoms or problems while taking methamphetamine hydrochloride tablets, especially seeing or hearing things that are not real, believing things that are not real, or are suspicious.

3. Circulation problems in fingers and toes[Peripheral vasculopathy, including Raynaud's phenomenon]:

- fingers or toes may feel numb, cool, painful
- fingers or toes may change color from pale, to blue, to red

Tell your doctor if you have or your child has numbness, pain, skin color change, or sensitivity to temperature in your fingers or toes.

Call your doctor right away if you have or your child has any signs of unexplained wounds appearing on fingers or toes while taking methamphetamine hydrochloride tablets.

What are methamphetamine hydrochloride tablets?

Methamphetamine hydrochloride tablets are a central nervous system stimulant prescription medicine. It is used for the treatment of Attention-Deficit Hyperactivity Disorder; (ADHD).

Methamphetamine hydrochloride tablets may help increase attention and decrease impulsiveness and hyperactivity in patients with ADHD.

Methamphetamine hydrochloride tablets should be used as a part of a total treatment program for ADHD that may include counseling or other therapies.

BOXED WARNING

Methamphetamine hydrochloride tablets are a federally controlled substance (CII) because it can be abused or lead to dependence. Keep methamphetamine hydrochloride tablets in a safe place to prevent misuse and abuse. Selling or giving away methamphetamine hydrochloride tablets may harm others, and is against the law.

Tell your or your child's doctor if you or your child have (or have a family history of) ever abused or been dependent on alcohol, prescription medicines or street drugs.

Who should not take methamphetamine hydrochloride tablets?

Methamphetamine hydrochloride tablets should not be taken if you or your child:

- have heart disease or hardening of the arteries
- have moderate to severe high blood pressure
- have hyperthyroidism
- have an eye problem called glaucoma
- are agitated
- have a history of drug abuse
- are taking or have taken within the past 14 days an antidepression medicine called a monoamine oxidase inhibitor or MAOI.
- are sensitive to, allergic to, or had a reaction to other stimulant medicines

Methamphetamine hydrochloride tablets are not recommended for use in children less than 6 years old in the treatment of ADHD.

Methamphetamine hydrochloride tablets may not be right for you or your child. Before starting methamphetamine hydrochloride tablets tell your or your child's doctor about all health conditions (or a family history of) including:

- heart problems, heart defects, high blood pressure
- mental problems including psychosis, mania, bipolar illness, or depression
- tics or Tourette's syndrome
- thyroid problems
- diabetes
- seizures or have had an abnormal brain wave test (EEG)
- circulation problems in fingers and toes

Tell your or your child's doctor if you or your child is pregnant, planning to become pregnant, or breastfeeding.

Can methamphetamine hydrochloride tablets be taken with other medicines?

Tell your or your child's doctor about all of the medicines that you or your child take including prescription and nonprescription medicines, vitamins, and herbal supplements.

Methamphetamine hydrochloride tablets and some medicines may interact with each other and cause serious side effects. Sometimes the doses of other medicines will need to be adjusted while taking methamphetamine hydrochloride tablets.

Your or your child's doctor will decide whether methamphetamine hydrochloride tablets can be taken with other medicines.

Especially tell your or your child's doctor if you or your child takes:

- anti-depression medicines including MAOIs
- anti-psychotic medicines
- blood pressure medicines
- insulin
- seizure medicines

Know the medicines that you or your child takes. Keep a list of your medicines with you to show your doctor and pharmacist.

Do not start any new medicine while taking methamphetamine hydrochloride tablets without talking to your or your child's doctor first.

How should methamphetamine hydrochloride tablets be taken?

- Take methamphetamine hydrochloride tablets exactly as prescribed.Your or your child's doctor may adjust the dose until it is right for you or your child.
- Methamphetamine hydrochloride tablets are usually taken 1 or 2 times each day.
- From time to time, your or your child's doctor may stop methamphetamine hydrochloride tablets treatment for a while to check ADHD symptoms.
- Your or your child's doctor may do regular checks of the blood, heart, and blood pressure while taking methamphetamine hydrochloride tablets. Children should have their height and weight checked often while taking methamphetamine hydrochloride tablets. Methamphetamine hydrochloride tablets treatment may be stopped if a problem is found during these check-ups.
- If you or your child takes too much methamphetamine hydrochloride tablets or overdoses, call your or your child's doctor or poison control center right away, or get emergency treatment.

What are possible side effects of methamphetamine hydrochloride tablets?

See " What is the most important information I should know about methamphetamine hydrochloride tablets?" for information on reported heart and mental problems.

Other serious side effects include:

- slowing of growth (height and weight) in children
- seizures, mainly in patients with a history of seizures
- eyesight changes or blurred vision

Common side effects include:

- fast heart beat
- tremors
- trouble sleeping
- stomach upset
- dry mouth

- decreased appetite
- headache
- dizziness
- weight loss

Methamphetamine hydrochloride tablets may affect your or your child's ability to drive or do other dangerous activities.

Talk to your or your child's doctor if you or your child has side effects that are bothersome or do not go away.

This is not a complete list of possible side effects.

Ask your or your child's doctor or pharmacist for more information.

Call your or your child's doctor for medical advice about side effects. You may report side effects to FDA at 1-800-FDA-1088 or www.fda.gov/medwatch or Mayne Pharma at 1-844-825-8500.

How should I store methamphetamine hydrochloride tablets?

- Store methamphetamine hydrochloride tablets in a safe place. Store at 20° to 25°C (68° to 77°F). [See USP Controlled Room Temperature.] Protect from light.
- Keep methamphetamine hydrochloride tablets and all medicines out of the reach of children.

General information about methamphetamine hydrochloride tablets:

Medicines are sometimes prescribed for purposes other than those listed in a Medication Guide. Do not use methamphetamine hydrochloride tablets for a condition for which it was not prescribed. Do not give methamphetamine hydrochloride tablets to other people, even if they have the same condition. It may harm them and it is against the law.

This Medication Guide summarizes the most important information about methamphetamine hydrochloride tablets. If you would like more information, talk with your or your child's doctor. You can ask your or your child's doctor or pharmacist for information about methamphetamine hydrochloride tablets that was written for healthcare professionals.

For more information about methamphetamine hydrochloride tablets, contact Mayne Pharma at 1-844-825-8500.

What are the ingredients in methamphetamine hydrochloride tablets?

Active Ingredient:methamphetamine hydrochloride, USP

Inactive Ingredients:Corn starch, lactose monohydrate, stearic acid and talc

This Medication Guide has been approved by the U.S. Food and Drug Administration.

Medication Guides available at products.maynepharma.com or call 1-844-825-8500.

Manufactured by:
Mayne Pharma
Greenville, NC 27834

61169
Rev. 03/2022

PRINCIPAL DISPLAY PANEL - 5 mg Tablet Bottle Label

NDC 68308-115-01

Methamphetamine
Hydrochloride
Tablets, USP

CII

5 mg

PHARMACIST: Dispense the
accompanying Medication Guide to
each patient.

Rx Only

100 Tablets

mayne pharma